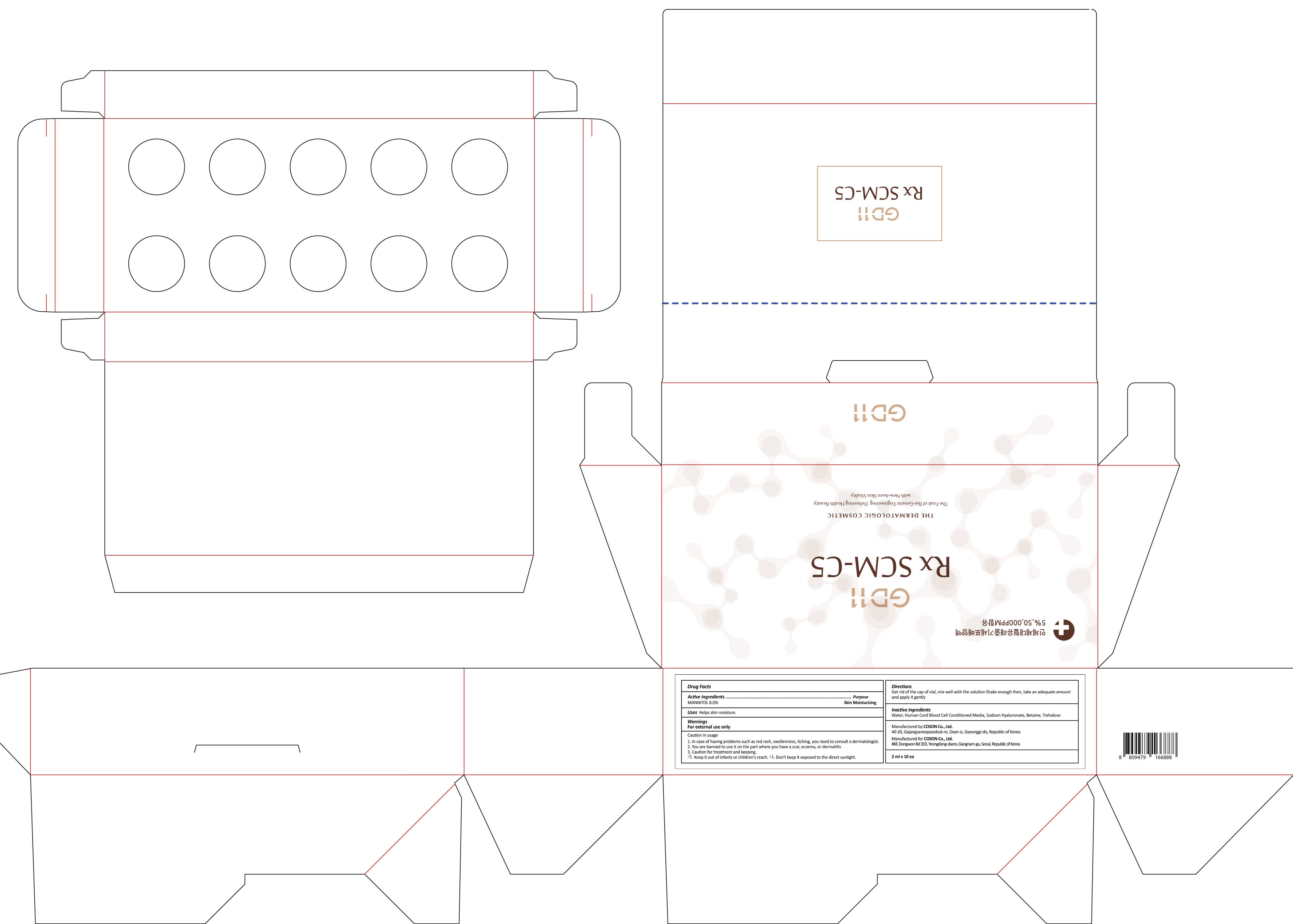 DRUG LABEL: GD11 Rx SCM C5
NDC: 62171-100 | Form: LIQUID
Manufacturer: Coson Co., Ltd.
Category: otc | Type: HUMAN OTC DRUG LABEL
Date: 20170824

ACTIVE INGREDIENTS: MANNITOL 0.10 g/2 mL
INACTIVE INGREDIENTS: Water; Betaine

ACTIVE INGREDIENT

Active ingredients: MANNITOL 8.0%

INACTIVE INGREDIENT

Inactive ingredients: Water, Human Cord Blood Cell Conditioned Media, Sodium Hyaluronate, Betaine, Trehalose

PURPOSE

Purpose: Skin Moisturizing

WARNINGS

Warnings: For external use only

Caution in usage 1. In case of having problems such as red rash, swollenness, itching, you need to consult a dermatologist. 2. You are banned to use it on the part where you have a scar, eczema, or dermatitis 3. Caution for treatment and keeping. - Keep it out of infants or children's reach. - Don't keep it exposed to the direct sunlight

KEEP OUT OF REACH OF CHILDREN

Keep it out of infants or children's reach.

Uses

Uses: Helps skin moisture.

Directions

Directions: Get rid of the cap, replace with the enclosed white plastic cap, take adequate amount apply it gently